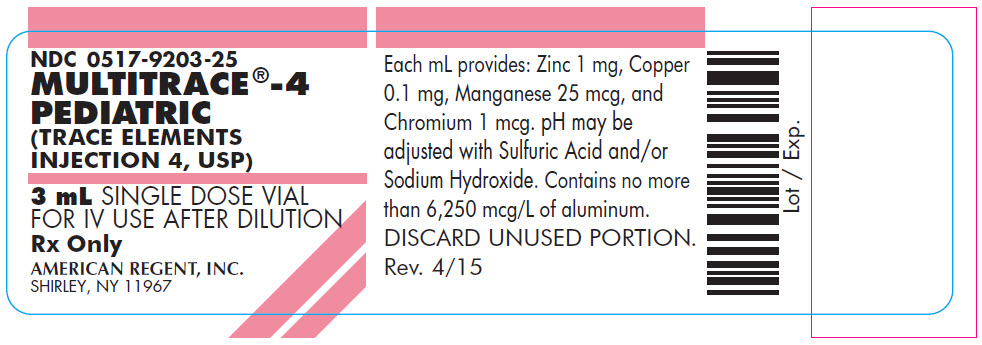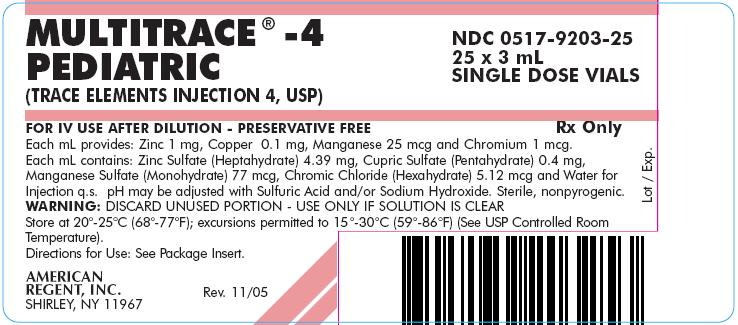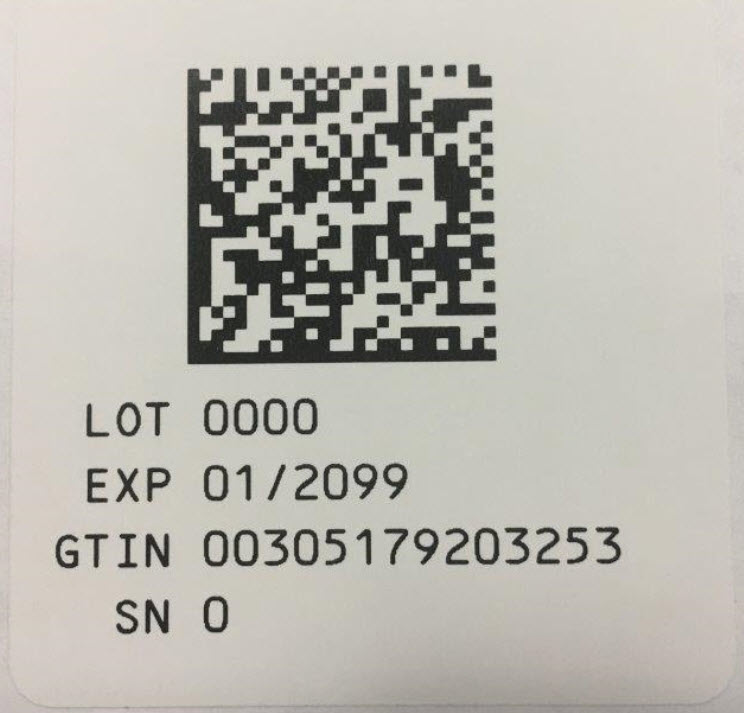 DRUG LABEL: Multitrace -4 Pediatric
NDC: 0517-9203 | Form: INJECTION, SOLUTION, CONCENTRATE
Manufacturer: American Regent, Inc.
Category: prescription | Type: HUMAN PRESCRIPTION DRUG LABEL
Date: 20190425

ACTIVE INGREDIENTS: ZINC SULFATE HEPTAHYDRATE 4.39 mg/1 mL; CUPRIC SULFATE 0.4 mg/1 mL; MANGANESE SULFATE 77 ug/1 mL; CHROMIC CHLORIDE 5.12 ug/1 mL
INACTIVE INGREDIENTS: SULFURIC ACID; SODIUM HYDROXIDE; WATER

MULTITRACE®- 4 PEDIATRIC
(TRACE ELEMENTS INJECTION 4, USP)

FOR IV USE AFTER DILUTION

Rx Only

DESCRIPTION

MULTITRACE® - 4 PEDIATRIC (TRACE ELEMENTS INJECTION 4, USP) is a sterile, nonpyrogenic solution containing four Trace Elements for use as an additive for Total Parenteral Nutrition (TPN).

Each mL provides: Zinc 1 mg, Copper 0.1 mg, Manganese 25 mcg and Chromium 1 mcg. Each mL contains: Zinc Sulfate Heptahydrate 4.39 mg (equivalent to 1 mg Zinc); Cupric Sulfate Pentahydrate 0.4 mg (equivalent to 0.1 mg Copper); Manganese Sulfate Monohydrate 77 mcg (equivalent to 25 mcg Manganese); Chromic Chloride Hexahydrate 5.12 mcg (equivalent to 1 mcg Chromium); and Water for Injection, q.s. pH of the solution may have been adjusted with sulfuric acid and/or sodium hydroxide. Preservative Free.

CLINICAL PHARMACOLOGY

ZINC has been identified as a cofactor for over 70 different enzymes, including carbonic anhydrase, alkaline phosphatase, lactic dehydrogenase and both RNA and DNA polymerase. Zinc facilitates wound healing, helps maintain normal growth rates, normal skin hydration and senses of taste and smell.

Providing zinc during TPN prevents development of the following deficiency symptoms: Parakeratosis, hypogeusia, anorexia, dysosmia, geophagia, hypogonadism, growth retardation and hepatosplenomegaly. At plasma levels below 20 mcg zinc/100 mL, dermatitis followed by alopecia has been reported for TPN patients.

COPPER is essential as a cofactor for serum ceruloplasmin, an oxidase necessary for proper formation of the iron carrier protein, transferrin. Copper also helps maintain normal rates of red and white blood cell formation. Scorbutic type bone changes seen in infants fed exclusively with copper-poor cow's milk are believed due to decreased activity of ascorbate oxidase, a cuproenzyme.

Providing copper during TPN prevents development of the following deficiency symptoms: leukopenia, neutropenia, anemia, depressed ceruloplasmin levels, impaired transferrin formation and secondary iron deficiency.

MANGANESE is an activator for enzymes such as polysaccharide polymerase, liver arginase, cholinesterase and pyruvate carboxylase.

Providing manganese during TPN prevents development of the following deficiency symptoms: nausea and vomiting, weight loss, dermatitis, and changes in growth and color of hair.

CHROMIUM (trivalent) is part of glucose tolerance factor, and activator insulin-mediated reactions. Chromium helps to maintain normal glucose metabolism and peripheral nerve function.

Providing chromium during TPN prevents development of the following deficiency symptoms: impaired glucose tolerance, ataxia, peripheral neuropathy, and a confusional state similar to mild/moderate hepatic encephalopathy.

INDICATIONS AND USAGE

This formulation is indicated for use as a supplement to intravenous solutions given for TPN for children up to 11 years of age. Administration of the solution in TPN solutions helps to maintain plasma levels of zinc, copper, manganese, and chromium and to prevent depletion of endogenous stores of these trace elements and subsequent deficiency symptoms.

CONTRAINDICATIONS

MULTITRACE® - 4 PEDIATRIC should not be given undiluted by direct injection into a peripheral vein because of the potential of infusion phlebitis.

WARNINGS

Copper and Manganese are eliminated via the bile. In patients with severe liver dysfunction and/or biliary tract obstruction, decreasing or omitting copper and manganese supplements entirely may be necessary.

This product contains aluminum that may be toxic. Aluminum may reach toxic levels with prolonged parenteral administration if kidney function is impaired. Premature neonates are particularly at risk because their kidneys are immature, and they require large amounts of calcium and phosphate solutions, which contain aluminum.

Research indicates that patients with impaired kidney function, including premature neonates, who receive parenteral levels of aluminum at greater than 4 to 5 mcg/kg/day accumulate aluminum at levels associated with central nervous system and bone toxicity. Tissue loading may occur at even lower rates of administration.

PRECAUTIONS

Before administering MULTITRACE® - 4 PEDIATRIC in TPN solutions, the physician must assess the metabolic requirements for trace elements and disease state of the patient. Frequent determinations of serum levels of the various trace elements are suggested as a guideline for adjusting the dosage or completely omitting the solution. ZINC is eliminated via the intestine and kidneys. The possibility of retention should be considered in patients with malfunctioning excretory routes. COPPER and MANGANESE are eliminated via the bile, therefore, the possibility of the retention of these elements should be considered in patients with biliary obstruction. Ancillary routes of MANGANESE excretion, however, include pancreatic juice, or reabsorption into the lumen of duodenum, jejunum, or ileum.

In assessing the contribution of CHROMIUM supplements to maintenance of normal glucose homeostasis, consideration should be given to the possibility that the patient may be diabetic, in which case oral or intravenous antidiabetic medication may be indicated.

Pregnancy

Teratogenic Effects

Pregnancy Category C: Safety for use in pregnancy has not been established. Use of MULTITRACE®- 4 PEDIATRIC in women of childbearing potential requires that anticipated benefits be weighed against possible hazards.

ADVERSE REACTIONS

The amounts of ZINC, COPPER, MANGANESE, AND CHROMIUM in the solution are very small and toxicity symptoms due to these trace elements at suggested dosage levels are considered unlikely to occur.

OVERDOSAGE

Symptoms of ZINC overdose resulting from oral ingestion of Zinc Sulfate in large amounts have resulted in death. Symptoms included nausea, vomiting, dehydration, electrolyte imbalances, dizziness, abdominal pain, lethargy and incoordination. Single intravenous doses of 1 to 2 mg zinc/kg body weight have been given to adult leukemia patients without toxic manifestations. Normal plasma levels for Zinc vary from approximately 88 to 112 mcg/100 mL. Plasma levels sufficient to produce symptoms of toxic manifestations are not known. Calcium supplements may confer a protective effect against Zinc toxicity.

Symptoms of COPPER toxicity reported in literature include prostration, behavior change, diarrhea, progressive marasmus, hypotonia, photophobia and peripheral edema. D-penicillamine has been reported effective as an antidote.

MANGANESE toxicity has not been reported in patients receiving TPN. Neither have reports of manganese toxicity from excessive intake in foods and/or beverages been published.

Symptoms of CHROMIUM toxicity include nausea, vomiting, ulcers and gastrointestinal tract, renal and hepatic damage, and abnormalities of the central nervous system culminating in convulsions and coma. Trivalent Chromium administered intravenously to TPN patients has been shown to be nontoxic when given at dosage levels up to 250 mcg/day for two consecutive weeks.

DOSAGE AND ADMINISTRATION

Each mL of the solution provides Zinc 1 mg, Copper 0.1 mg, Manganese 25 mcg, and Chromium 1 mcg, and is administered intravenously only after dilution to a minimum of 1:200. The suggested dosage ranges for the four trace elements are:

ZINC: For full term infants and children, 100 mcg zinc/kg/day is recommended. For premature infants (birth weight less than 1500 g) up to 3 kg in body weight, 300 mcg zinc/kg/day is suggested.

COPPER: For pediatric patients, the suggested additive dosage level is 20 mcg copper/kg/day. The normal plasma range for copper is approximately 80 to 160 mcg/100 mL.

MANGANESE: For pediatric patients, a dosage level of 2 to 10 mcg manganese/kg/day is recommended.

CHROMIUM: For pediatric patients, the suggested additive dosage level is 0.14 to 0.20 mcg/kg/day.

Periodic monitoring of plasma levels of Zinc, Copper, Manganese, and Chromium is suggested as a guideline for administration.

Aseptic addition of MULTITRACE® - 4 PEDIATRIC to parenteral nutrition solutions under a laminar flow hood is recommended. The trace elements present in MULTITRACE® - 4 PEDIATRIC are physically compatible with the electrolytes and vitamins usually present in parenteral nutrition formulations.

Do not directly mix ascorbic acid injection with copper or selenium containing parenteral products in the same syringe or vial, as this admixture may cause the formation of an insoluble precipitate.

Parenteral drug products should be inspected visually for particulate matter and discoloration prior to administration, whenever solution and container permit.

Store at 20°-25°C (68°-77°F); excursions permitted to 15°-30°C (59°-86°F) (See USP Controlled Room Temperature).

HOW SUPPLIED

MULTITRACE®- 4 PEDIATRIC (TRACE ELEMENTS INJECTION 4, USP)

Each mL provides: Zinc 1 mg, Copper 0.1 mg, Manganese 25 mcg, and Chromium 1 mcg.

NDC 0517-9203-25 3 mL Single Dose Vial Packaged in boxes of 25

AMERICAN
REGENT, INC.
SHIRLEY, NY 11967

IN9203
Rev. 8/18

PACKAGE LABEL.PRINCIPAL DISPLAY PANEL

Container
NDC 0517-9203-25
MULTITRACE -4 PEDIATRIC
(TRACE ELEMENTS INJECTION 4, USP)

3 mL SINGLE DOSE VIAL

FOR IV USE AFTER DILUTION

Rx Only
AMERICAN REGENT, INC.
SHIRLEY, NY 11967

Carton

MULTITRACE -4 PEDIATRIC
(TRACE ELEMENTS INJECTION 4, USP)

NDC 0517-9203-25
25 x 3 mL
SINGLE DOSE VIALS

FOR IV USE AFTER DILUTION - PRESERVATIVE FREE

Rx Only

Each mL provides: Zinc 1 mg, Copper 0.1 mg, Manganese 25 mcg and Chromium 1 mcg. Each mL contains: Zinc Sulfate (Heptahydrate) 4.39 mg, Cupric Sulfate (Pentahydrate) 0.4 mg, Manganese Sulfate (Monohydrate) 77 mcg, Chromic Chloride (Hexahydrate) 5.12 mcg and Water for Injection q.s. pH may be adjusted with Sulfuric Acid and/or Sodium Hydroxide. Sterile, nonpyrogenic.
WARNING: DISCARD UNUSED PORTION - USE ONLY IF SOLUTION IS CLEAR.
Store at 20°-25°C (68°-77°F); excursions permitted to 15°-30°C (59°-86°F) (See USP Controlled Room Temperature).
Directions for Use: See Package Insert.

AMERICAN
REGENT, INC.
SHIRLEY, NY 11967

Rev. 11/05